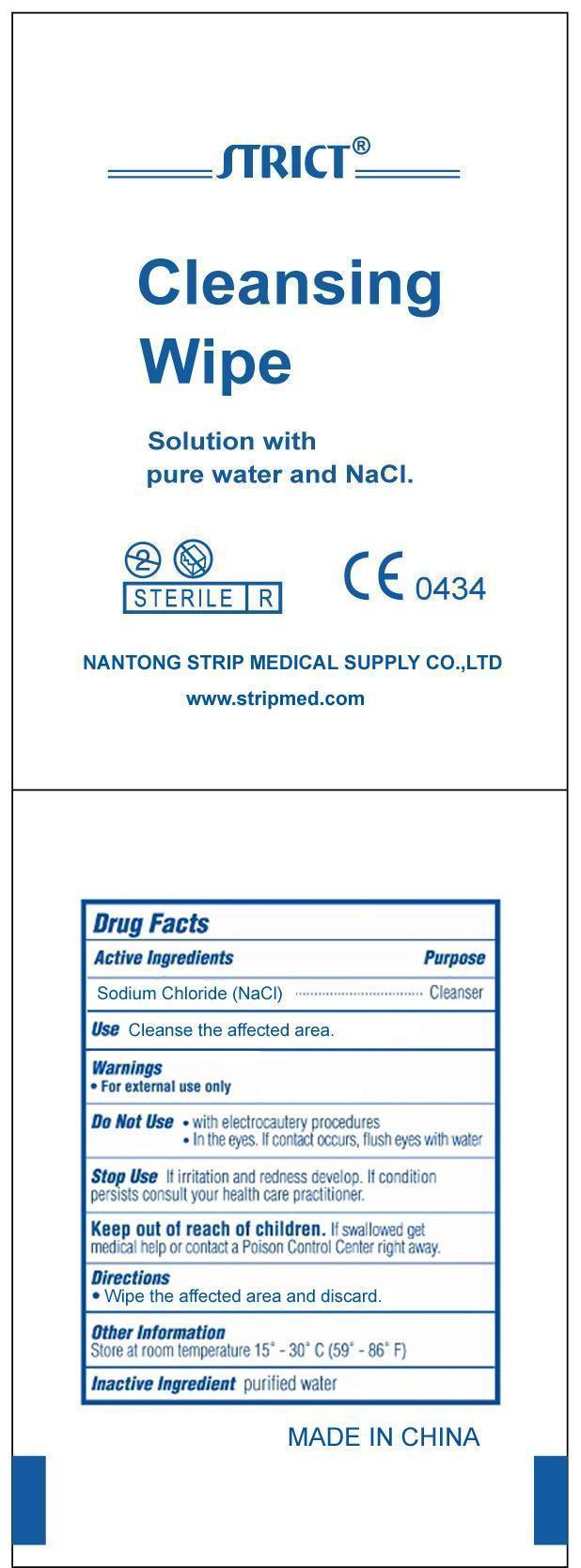 DRUG LABEL: Cleansing Wipe / Tube
NDC: 35617-399 | Form: SWAB
Manufacturer: NANTONG STRIP MEDICAL SUPPLY CO.,LTD.
Category: otc | Type: HUMAN OTC DRUG LABEL
Date: 20120817

ACTIVE INGREDIENTS: SODIUM CHLORIDE 0.9 g/100 mL
INACTIVE INGREDIENTS: WATER

Drug Facts Alcohol Swabsticks

Active Ingredient

Sodium chloride (NaCl) 0.9%

Purpose

Cleansing

Use

Clean affected area

Warnings

For external use only .

Keep out of reach of children.

Directions

Clean affected area

Inactive Ingredients

Purified Water